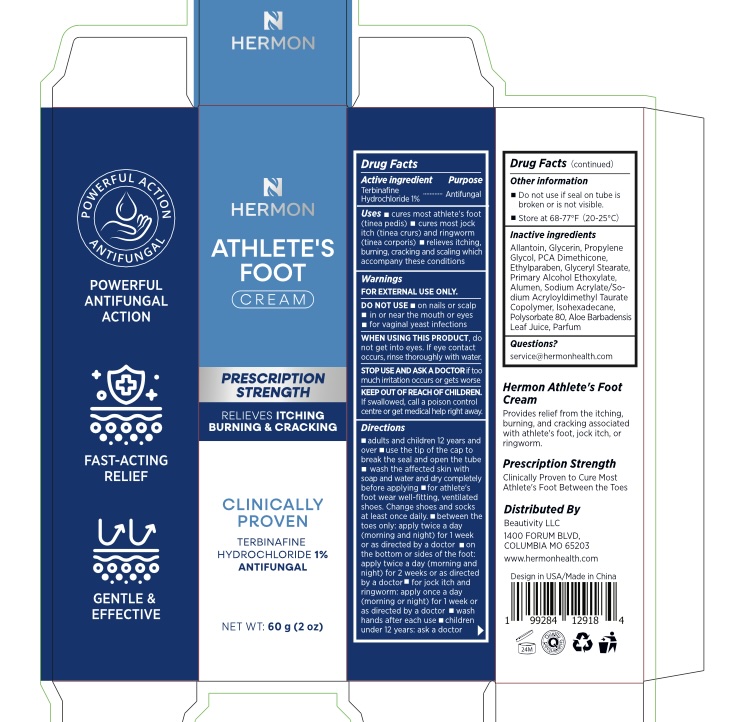 DRUG LABEL: Athlete Foot Cream
NDC: 85398-006 | Form: CREAM
Manufacturer: Beautivity LLC
Category: otc | Type: HUMAN OTC DRUG LABEL
Date: 20260302

ACTIVE INGREDIENTS: TERBINAFINE HYDROCHLORIDE 1 g/100 g
INACTIVE INGREDIENTS: POTASSIUM ALUM; SODIUM ACRYLATE/SODIUM ACRYLOYLDIMETHYLTAURATE COPOLYMER (4000000 MW); GLYCERIN; GLYCERYL STEARATE; ALOE BARBADENSIS LEAF JUICE; DIMETHICONE; C12-15 PARETH-7; ALLANTOIN; POLYSORBATE 80; PROPYLENE GLYCOL; ETHYLPARABEN; ISOHEXADECANE

Update-85398-006-01

ACTIVE INGREDIENT

Terbinafine Hydrochloride 1%

PURPOSE

Antifungal

INDICATIONS AND USAGE

- cures most athlete's foot (tinea pedis)
- cures most jock itch (tinea crurs) and ringworm (tinea corporis)
- relieves itching, burning, cracking and scaling which accompany these conditions

WARNINGS

For external use only

DO NOT USE

- on nails or scalp
- in or near the mouth or eyes
- for vaginal yeast infections

WHEN USING

do not get into eyes, if eye contact occurs, rinse thoroughly with water.

stop use and ask a doctor if too much irritation occurs or gets worse.

KEEP OUT OF REACH OF CHILDREN

if swallowed, call a poison control centre or get medical help right away.

DOSAGE AND ADMINISTRATION

■ adults and children 12 years and over
■ use the tip of the cap to break the seal and open the tube
■ wash the affected skin with soap and water and dry completely before applying
■ for athlete’s foot wear well-fitting, ventilated shoes. Change shoes and socks at least once daily.
■ between the toes only: apply twice a day (morning and night) for 1 week or as directed by a doctor
■ on the bottom or sides of the foot: apply twice a day (morning and night) for 2 weeks or as directed by a doctor
■ for jock itch and ringworm: apply once a day (morning or night) for 1 week or as directed by a doctor
■ wash hands after each use
■ children under 12 years: ask a doctor

■ Do not use if seal on tube is broken or is not visible.
■ Store at 68–77°F (20–25°C)

INACTIVE INGREDIENT

Allantoin, Glycerin, Propylene Glycol, PCA Dimethicone, Ethylparaben, Glyceryl Stearate, Primary Alcohol Ethoxylate, Alumen, Sodium Acrylate/Sodium Acryloyldimethyl Taurate Copolymer, Isohexadecane, Polysorbate 80, Aloe Barbadensis Leaf Juice, Parfum

QUESTIONS

service@hermonhealth.com